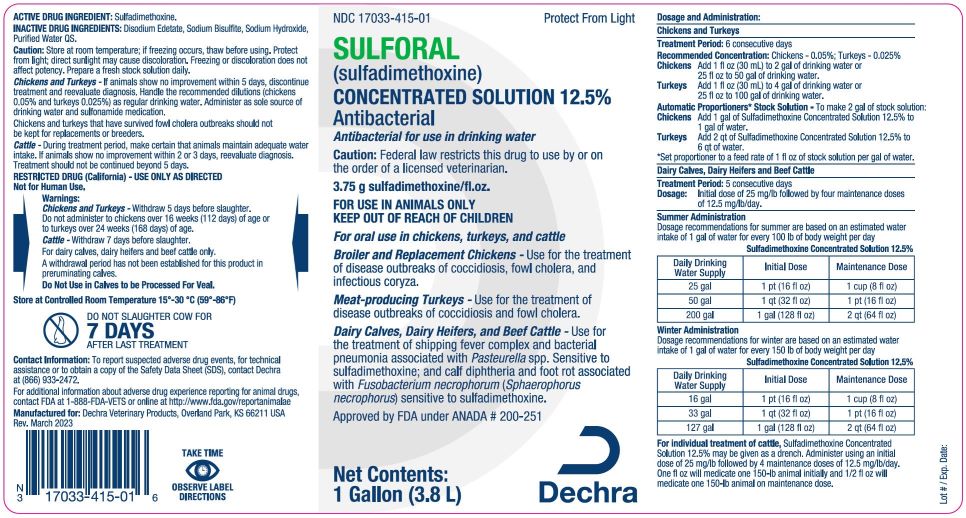 DRUG LABEL: Sulforal
NDC: 17033-415 | Form: SOLUTION
Manufacturer: Dechra Veterinary Products
Category: animal | Type: PRESCRIPTION ANIMAL DRUG LABEL
Date: 20230530

ACTIVE INGREDIENTS: Sulfadimethoxine 125 mg/1 mL

Sulforal (sulfadimethoxine)

DESCRIPTION

Concentrated Solution 12.5%

Antibacterial for use in drinking water.

3.75g sulfadimethoxine/fl.oz. / 1 Gallon (3.8L)

CAUTION: Federal (USA) law restricts this drug to use by or on the order of a licensed veterinarian.

Approved by FDA under ANADA #200-251

Protect From Light - For oral use in chickens, turkeys, and cattle.

INDICATIONS:

Broiler and Replacement Chickens - Use for the treatment of disease outbreaks of coccidiosis, fowl cholera, and infectious coryza.

Meat-producing Turkeys - Use for the treatment of disease outbreaks of coccidiosis, and fowl cholera.

Dairy Calves, Dairy Heifers, and Beef Cattle - Use for the treatment of shipping fever complex and bacterial pneumonia associated with Pasteurella spp. sensitive to sulfadimethoxine; and calf diphtheria and foot rot associated with Fusobacterium necrophorum (Sphaerophorus necrophorus) sensitive to sulfadimethoxine.

WARNINGS AND PRECAUTIONS

CAUTION: Store at room temperature; if freezing occurs, thaw before using. Protect from light; direct sunlight may cause discoloration. Freezing or discoloration does not affect potency. Prepare a fresh stock solution daily.

Chickens and Turkeys-If animals show no improvement within 5 days, discontinue treatment and reevaluate diagnosis. Handle the recommended dilutions (chickens 0.05% and turkeys 0.0.25%) as regular drinking water. Administer as sole source of drinking water and sulfonamide medication.

Chickens and turkeys that have survived fowl cholera outbreaks should not be kept for replacements or breeders.

Cattle- During treatment period, make certain that animals maintain adequate water intake. If animals show no improvement within 2 or 3 days, reevaluate diagnosis. Treatment should not be continued beyond 5 days.

Restricted Drug (California) - Use Only as Directed. Not for Human Use.

CONTACT INFORMATION: To report suspected adverse drug events, for technical assistance or to obtain a copy of the Safety Data Sheet (SDS), contact Dechra at (866) 933-2472.

For additional information about adverse drug experience reporting for animal drugs, contact FDA at 1-888-FDA-VETS or online at http://www.fda.gov/reportanimalae

WARNINGS:

Chickens and Turkeys-Withdraw 5 days before slaughter. Do not administer to chickens over 16 weeks (112 days) of age or to turkeys over 24 weeks (168 days) of age.

Cattle-Withdraw 7 days before slaughter. For dairy calves, dairy heifers and beef cattle only.

A withdrawal period has not been established for this product in preruminating calves.

Do Not Use in Calves to be Processed For Veal

DO NOT SLAUGHTER COW FOR 7 DAYS AFTER LAST TREATMENT

Dosage and Administration:

Chickens and Turkeys

Treatment Period: 6 consecutive days
Recommended Concentration: Chickens -0.05%; Turkeys -0.025%
Chickens Add 1 fl oz (30 mL) to 2 gal of drinking water or
25 fl oz to 50 gal of drinking water.
Turkeys Add 1 fl oz (30 mL) 4 gal of drinking water or
25 fl oz to 100 gal of drinking water.
Automatic Proportioners* Stock Solution - To make 2 gal of stock solution:
Chickens Add 1 gal of Sulforal Concentrated Solution 12.5% to 1gal of water.
Turkeys Add 2 qt of Sulforal Concentrated Solution 12.5% to 6 qt of water.
*Set proportioner to a feed rate of 1 fl oz of stock solution per gal of water

Dairy Calvers, Dairy Heifers and Beef Cattle

Treatment Period: 5 consecutive days
Dosage: Initial dose of 25 mg/lb followed by four maintenance dose
of 12.5 mg/lb/day.

Summer Administration
Dosage recommendations for summer are based on an estimated water intake of 1 gal of water for every 100 lb of body weight per day.

Sulfadimethoxine Concentrated Solution 12.5%

Daily Drinking Water Supply Initial Dose Maintenance Dose

25 gal 1 pt (16 fl oz) 1 cup (8 fl oz)
50 gal 1 qt (32 fl oz) 1 pt (16 fl oz)
200 gal 1 gal (128 fl oz) 2 qt (64 fl oz)

Winter Administration
Dosage recommendations for summer are based on an estimated water intake of 1 gal of water for every 150 lb of body weight per day.

Sulfadimethoxine Concentrated Solution 12.5%

Daily Drinking Water Supply Initial Dose Maintenance Dose

16 gal 1 pt (16 fl oz) 1 cup (8 fl oz)
33 gal 1 qt (32 fl oz) 1 pt (16 fl oz)
127 gal 1 gal (128 fl oz) 2 qt (64 fl oz)

For individual treatment of cattle, Sulfadimethoxine Concentrated Solution 12.5% may be given as a drench. Administer using an initial dose of 25 mg/lb followed by 4 maintenance doses of 12.5 mg/lb/day. One fl oz will medicated one 150-lb animal initially and 1/2 fl oz will medicate one 150-lb animal on maintenance dose.

STORAGE AND HANDLING

STORAGE: Store at Controlled Room Temperature 15°-30°C (59°-86°F).

Manufactured for:
Dechra Veterinary Products, LLC
Overland Park, KS 66211

Rev. 05/2023